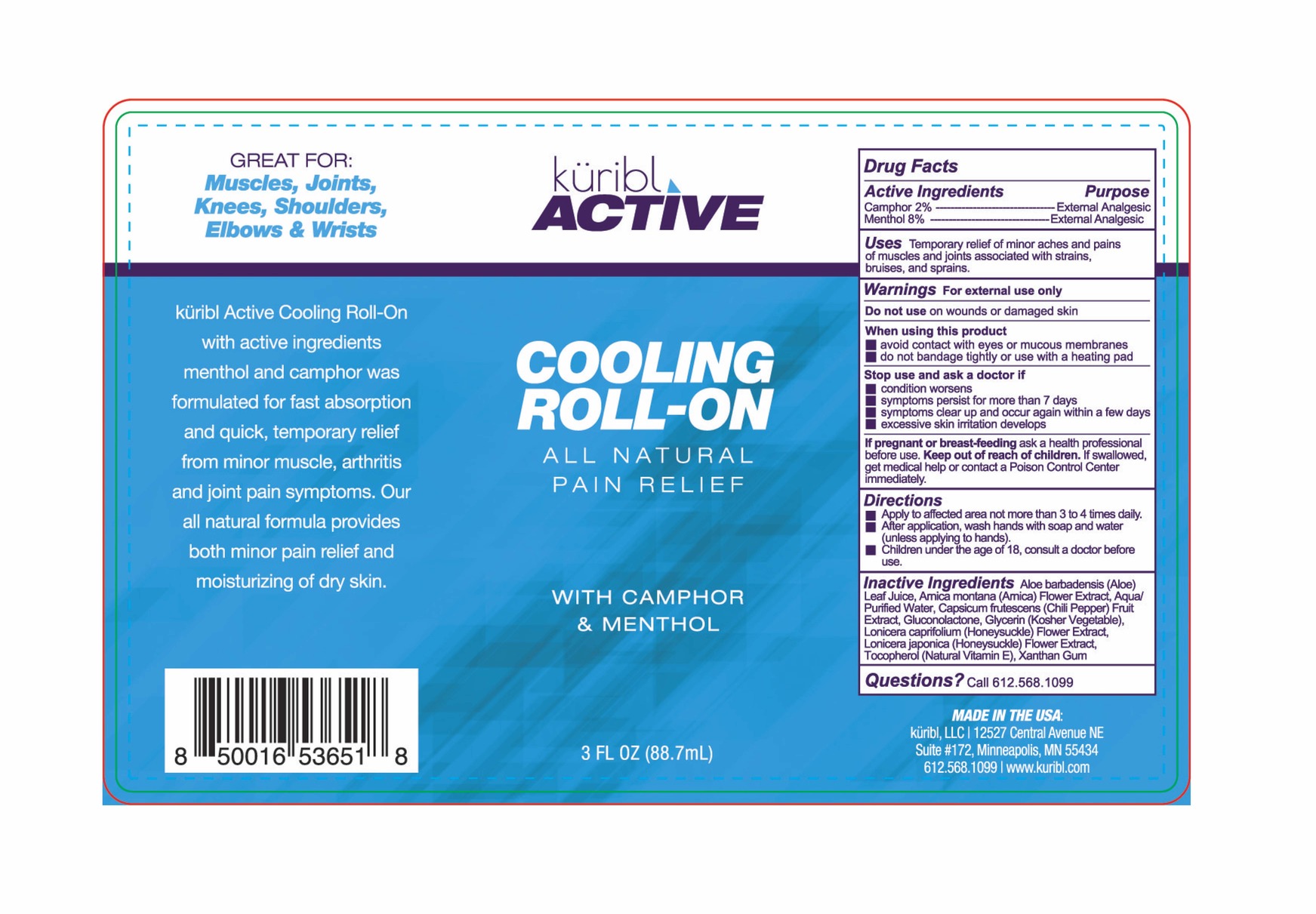 DRUG LABEL: Kuribl Active Cooling Roll-on
NDC: 83111-001 | Form: LIQUID
Manufacturer: Radiance Beauty & Wellness Inc. dba Saavy Naturals
Category: otc | Type: HUMAN OTC DRUG LABEL
Date: 20230110

ACTIVE INGREDIENTS: MENTHOL 8 g/100 mL; CAMPHOR (NATURAL) 2 g/100 mL
INACTIVE INGREDIENTS: GLUCONOLACTONE; LONICERA JAPONICA FLOWER; ALOE VERA LEAF; TABASCO PEPPER; WATER; TOCOPHEROL; ARNICA MONTANA FLOWER; GLYCERIN; XANTHAN GUM; LONICERA CAPRIFOLIUM FLOWER

Kuribl Active Cooling Roll-on

Active Ingredients Purpose

Camphor 2% External Analgesic

Menthol 8% External Analgesic

PURPOSE

Uses Temporary relief of minor aches and pains of muscles and joints associated with strains, bruises, and sprains.

Keep out of reach of children. If swallowed, get medical help or contact a Poison Control Center immediately.

Stop use and ask a doctor if

- condition worsen
- symptoms persist for more than 7 days
- symptoms clear up and occur again within a few days
- excessive skin irritation develops

Warnings For external use only

Do not use on wounds or damaged skin

When using this product

- avoid contact with eyes or mucous membranes
- do not bandage tightly or use with a heating pad

If pregnant or breast feeding ask a health professional before use

Directions

- Apply to affected area not more than 3 to 4 times daily
- After application, wash hands with soap and water (unless applying to hands)
- Children under the age of 18, consult a doctor before use

INACTIVE INGREDIENT

Inactive Ingredients Aloe barbadensis (Aloe) Leaf Juice, Arnica montana (Arnica) Flower Extract, Aqua/ Purified Water, Capsicum frutescens (Chili Pepper) Fruit Extract, Gluconolactone, Glycerin (Kosher Vegetable), Lonicera caprifolium (Honeysuckle) Flower Extract, Lonicera japonica (Honeysuckle) Flower Extract, Tocopherol (Natural Vitamin E), Xanthan Gum

PACKAGE LABEL

Kuribl Active

Cooling Roll-on

All Natural Pain Relief

with Camphor & Menthol

3 FL OZ (88.7 mL)